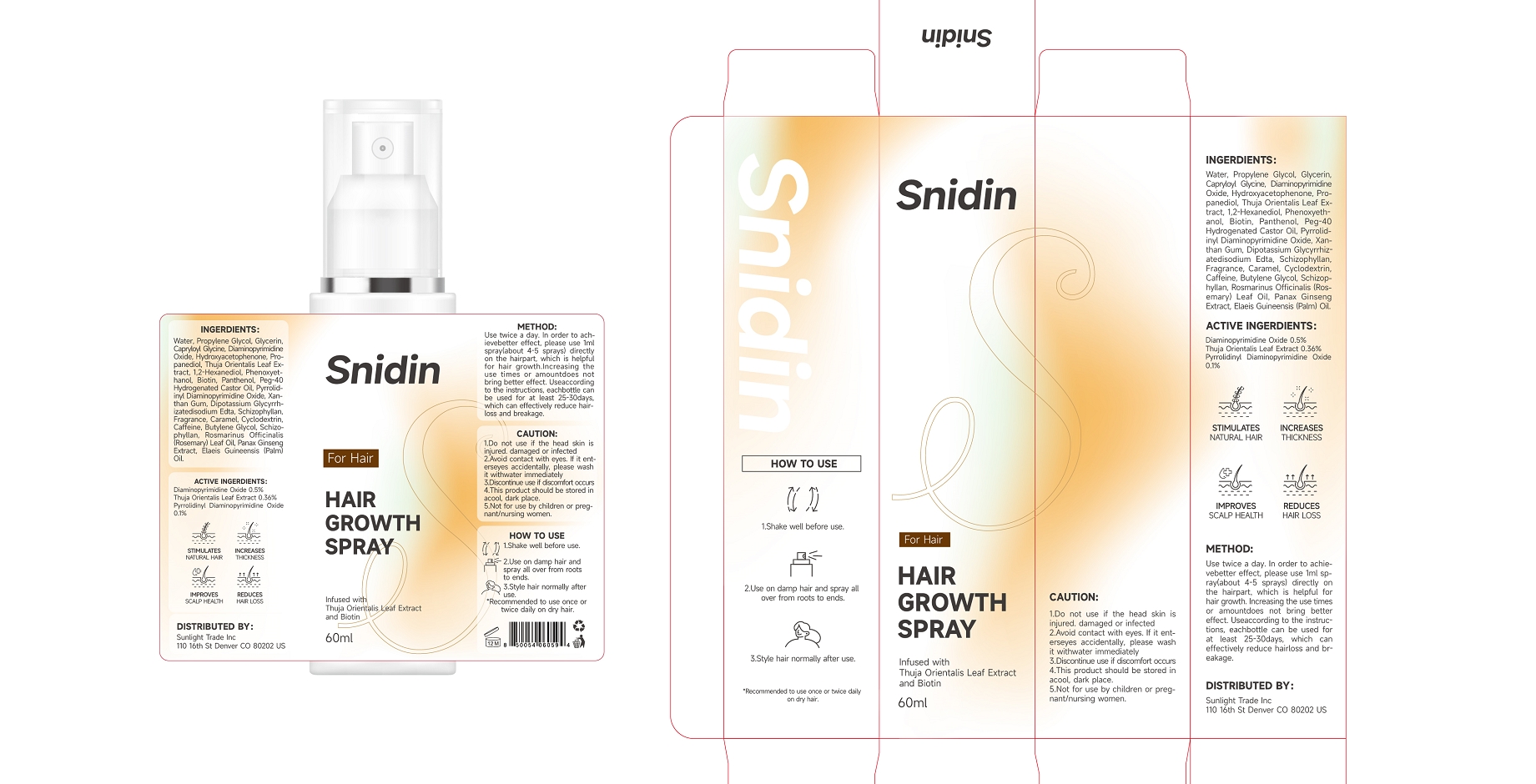 DRUG LABEL: Snidin
NDC: 84507-038 | Form: LIQUID
Manufacturer: Guangdong Miaolian Cosmetics Co., Ltd.
Category: otc | Type: HUMAN OTC DRUG LABEL
Date: 20250625

ACTIVE INGREDIENTS: PYRROLIDINYL DIAMINOPYRIMIDINE OXIDE 0.1 mg/100 mL; PLATYCLADUS ORIENTALIS LEAF 0.36 mg/100 mL; DIAMINOPYRIMIDINE OXIDE 0.5 mg/100 mL
INACTIVE INGREDIENTS: 1,2-HEXANEDIOL; PROPANEDIOL; PHENOXYETHANOL; SCHIZOPHYLLAN; ELAEIS GUINEENSIS (PALM) OIL; CAPRYLOYL GLYCINE; HYDROXYACETOPHENONE; XANTHAN GUM; FRAGRANCE CHOCOLATE ORC1600599; BUTYLENE GLYCOL; CAFFEINE; CYCLODEXTRIN; WATER; PROPYLENE GLYCOL; DIPOTASSIUM GLYCYRRHIZATE; CARAMEL; BIOTIN; EDETATE DISODIUM; PANAX GINSENG WHOLE; PEG-40 HYDROGENATED CASTOR OIL; ROSMARINUS OFFICINALIS (ROSEMARY) LEAF OIL; GLYCERIN; PANTHENOL

DOSAGE AND ADMINISTRATION

Use twice a day. In order to ach-ievebetter effect, please use 1mlspray(about 4-5 sprays) directlyon the hairpart, which is helpfulfor hair growth.Increasing theuse times or amountdoes notbring better effect. Useaccordingto the instructions, eachbottle canbe used for at least 25-30days,which can effectively reduce hair-loss and breakage.

INACTIVE INGREDIENT

WATER
PROPYLENE GLYCOL
PROPANEDIOL
PEG-40 HYDROGENATED CASTOR OIL
DISODIUM EDTA
GLYCERIN
CAPRYLOYL GLYCINE
HYDROXYACETOPHENONE
1,2-HEXANEDIOL
PANTHENOL
BIOTIN
PHENOXYETHANOL
SCHIZOPHYLLAN
XANTHAN GUM
DIPOTASSIUM GLYCYRRHIZATE
CARAMEL
FRAGRANCE
BUTYLENE GLYCOL
PANAX GINSENG EXTRACT
CAFFEINE
CYCLODEXTRIN
ROSMARINUS OFFICINALIS (ROSEMARY) LEAF OIL
ELAEIS GUINEENSIS (PALM) OIL

INDICATIONS AND USAGE

1.Shake well before use.

2.Use on damp hair andspray all over from rootsto ends.

3.Style hair normally afterUSe.Recommended to use once ortwice daily on dry hair.

WARNINGS

1.Do not use if the head skin isinjured. damaged or infected.

2.Avoid contact with eyes. lf it ent-erseyes accidentally, please washit withwater immediately.

3.Discontinue use if discomfort occurs.

4.This product should be stored inacool, dark place.

5.Not for use by children or preg-nant/nursing women.

KEEP OUT OF REACH OF CHILDREN

If swallowed, get medical help or contact a Poison Control Center right away.

ACTIVE INGREDIENT

THUJA ORIENTALIS LEAF EXTRACT--------- 0.36
DIAMINOPYRIMIDINE OXIDE --------- 0.5
PYRROLIDINYL DIAMINOPYRIMIDINE OXIDE --------- 0.1

PURPOSE

Hair growth